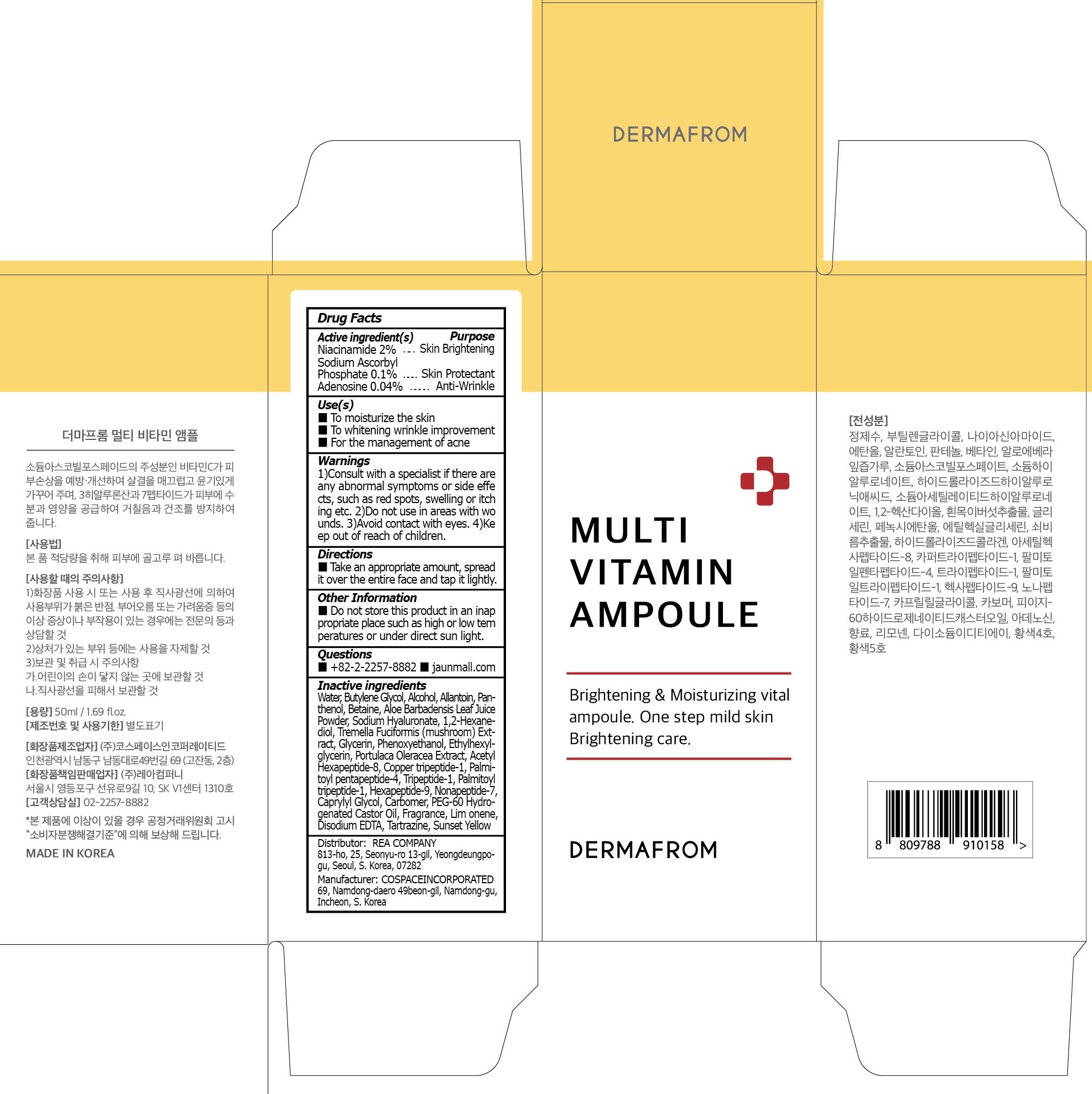 DRUG LABEL: DERMAFROM MULTI VITAMIN AMPOULE
NDC: 82916-150 | Form: LIQUID
Manufacturer: Rea Company
Category: otc | Type: HUMAN OTC DRUG LABEL
Date: 20221031

ACTIVE INGREDIENTS: Niacinamide 2.0 g/100 mL; Adenosine 0.04 g/100 mL
INACTIVE INGREDIENTS: Water; Butylene Glycol; Alcohol

ACTIVE INGREDIENTS

Niacinamide 2%
Sodium Ascorbyl Phosphate 0.1%
Adenosine 0.04%

PURPOSE

Skin Brightening
Skin Protectant
Anti-Wrinkle

Use(s)

■ To moisturize the skin
■ To whitening wrinkle improvement
■ For the management of acne

Warnings

1) Consult with a specialist if there are any abnormal symptoms or side effects, such as red spots, swelling or itching etc
2) Do not use in areas with wounds.
3) Avoid contact with eyes
4) Keep out of reach of children

KEEP OUT OF REACH OF CHILDREN

Directions

■ Take an appropriate amount, spread it over the entire face and tap it lightly

Other Information

■ Do not store this product in an inappropriate place such as high or low temperatures or under direct sun light

Questions

■ +82-2-2257-8882
■ jaunmall.com

Inactive ingredients

Water, Butylene Glycol, Alcohol, Allantoin, Panthenol, Betaine, Aloe Barbadensis Leaf Juice Powder, Sodium Hyaluronate, 1, 2-Hexanediol, Tremella Fuciformis (mushroom) Extract, Glycerin, Phenoxyethanol, Ethylhexylglycerin, Portulaca Oleracea Extract, Acetyl Hexapeptide-8, Copper tripeptide-1, Palmitoyl pentapeptide-4, Tripeptide-1, Palmitoyl tripeptide-1, Hexapeptide-9, Nonapeptide-7, Caprylyl Glycol, Carbomer, PEG-60 Hydrogenated Castor Oil, Fragrance, Lim onene, Disodium EDTA, Tartrazine, Sunset Yellow